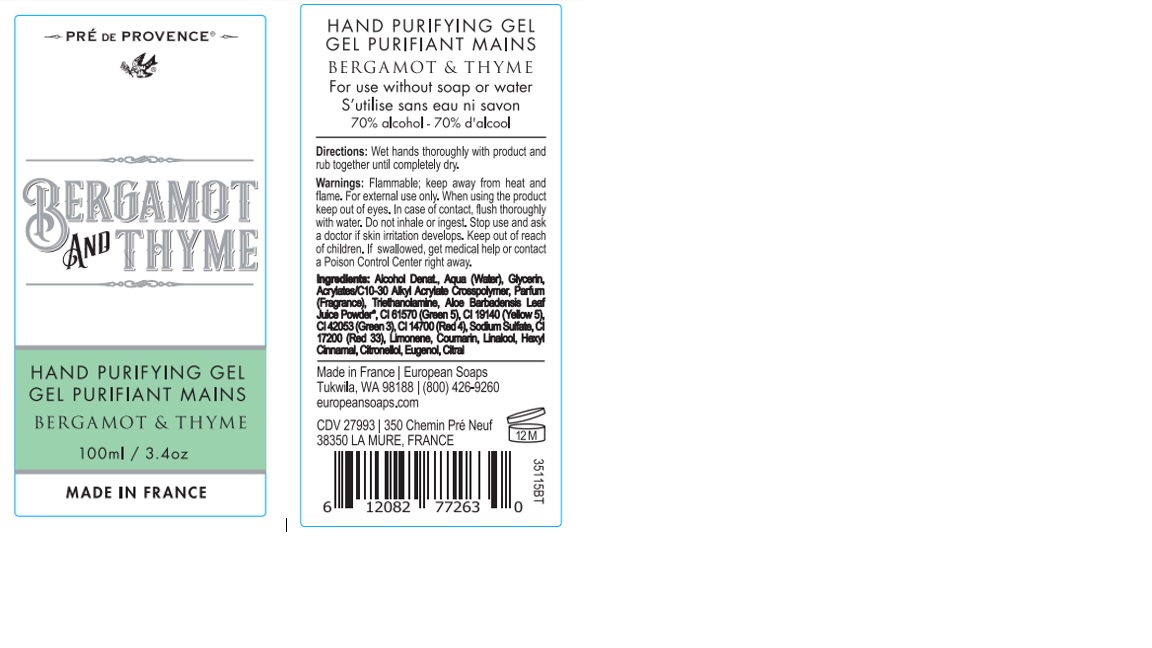 DRUG LABEL: 100ml BERG and THYME Hand purifying
NDC: 74819-0106 | Form: GEL
Manufacturer: LABORATOIRES BEA
Category: otc | Type: HUMAN OTC DRUG LABEL
Date: 20220627

ACTIVE INGREDIENTS: ALCOHOL 70 mL/100 mL
INACTIVE INGREDIENTS: TROLAMINE 0.15 mL/100 mL; ALOE 0.0005 mL/100 mL; GLYCERIN 2 mL/100 mL; CARBOMER INTERPOLYMER TYPE A (ALLYL SUCROSE CROSSLINKED) 0.55 mL/100 mL; WATER 25.3885 mL/100 mL

EUROPEAN SOAPS - 100ml BERG and THYME Hand purifying gel

Active Ingredient(s)

Ethyl Alcohol 70%

This is a hand sanitizer manufactured according to the Temporary Policy for Preparation of Certain Alcohol-Based Hand Sanitizer Products During the Public Health Emergency (CoViD-19); Guidance for Industry.

The hand sanitizer is manufactured using only the following United States Pharmacopoeia (USP) grade ingredients in the preparation of the product (percentage in final product formulation) consistent with World Health Organization (WHO) recommendations:

1. Alcohol (ethanol) (USP or Food Chemical Codex (FCC) grade) (80%, volume/volume (v/v)) in an aqueous solution denatured according to Alcohol and Tobacco Tax and Trade Bureau regulations in 27 CFR part 20.
2. Glycerol (1.45% v/v).
3. Hydrogen peroxide (0.125% v/v).
4. Sterile distilled water or boiled cold water.

The firm does not add other active or inactive ingredients. Different or additional ingredients may impact the quality and potency of the product.

Purpose

Antiseptic

Use

Hand Sanitizer to help reduce bacteria that potentially can cause disease. For use when soap and water are not available.

Warnings

For external use only. Flammable. Keep away from heat or flame. When using the product, keep out of eyes. Do not inhale or ingest.

Do not use

on open skin wounds - around eyes - in ears and mouth

When using this product keep out of eyes, ears, and mouth. In case of contact with eyes, flush thoroughly with water.

Stop use and ask a doctor if irritation or rash occurs. These may be signs of a serious condition.

Keep out of reach of children. If swallowed, get medical help or contact a Poison Control Center right away.

Directions

- Wet hands thoroughly with product and allow to dry without wiping.
- Supervise children under 6 years of age when using this product to avoid swallowing.
- Not recommended for infants

Other information

- Store between 15-30C (59-86F)
- Avoid freezing and excessive heat above 40C (104F)
- May discolor some fabrics
- Harmful to wood finishes and plastics

Inactive ingredients

Aqua (Water), Glycerin, Acrylates/C10-30 Alkyl Acrylate Crosspolymer, Parfum (Fragrance), Triethanolamine, Aloe Barbadensis Leaf Juice Powder